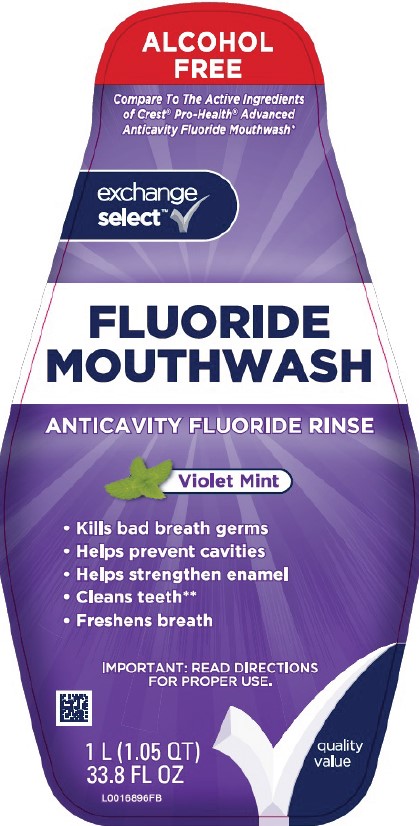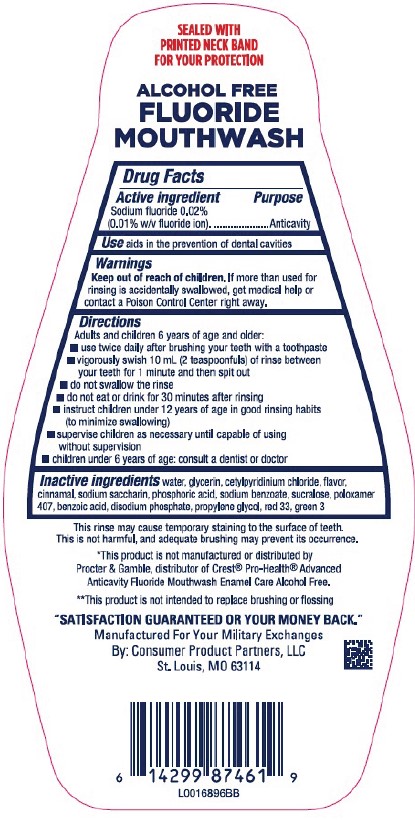 DRUG LABEL: Alcohol-Free Anticavity
NDC: 55301-482 | Form: LIQUID
Manufacturer: Your Military Exchanges
Category: otc | Type: HUMAN OTC DRUG LABEL
Date: 20260212

ACTIVE INGREDIENTS: SODIUM FLUORIDE 0.1 mg/1 mL
INACTIVE INGREDIENTS: WATER; GLYCERIN; CETYLPYRIDINIUM CHLORIDE; CINNAMALDEHYDE; SACCHARIN SODIUM; PHOSPHORIC ACID; SODIUM BENZOATE; SUCRALOSE; POLOXAMER 407; BENZOIC ACID; SODIUM PHOSPHATE, DIBASIC, ANHYDROUS; PROPYLENE GLYCOL; D&C RED NO. 33; FD&C GREEN NO. 3

Exchange Select 482.003/482AC
Alcohol Free Fluoride Violet Mint Mouthwash

TAMPER EVIDENT STATEMENT

SEALED WITH PRINTED NACKBAND FOR YOUR PROTECTION

Claim

ALCOHOL FREE

FLUORIDE MOUTHWASH

Active ingredient

Sodium fluoride 0.02% (0.01% w/v fluoride ion)

Purpose

Anticavity

Use

aids in the prevention of dental cavities

Warnings

for this product

Keep out of reach of children.

If more than used for rinsing is accidentally swallowed, get medical help or contact a Poison Control Center right away.

Directions

Adults and children 6 years of age and older:

- use twice daily after brushing your teeth with a toothpaste
- vigorously swish 10 mL (2 teaspoonfuls) of rinse between your teeth for 1 minute then spit out
- do not swallow the rinse
- do not eat or drink for 30 minutes after rinsing
- instruct children under 12 years of age in good rinsing habits (to minimize swallowing)
- supervise children as necessary until capable of using without supervision
- children under 6 years of age: consult a dentist or doctor

Inactive ingredients

water, glycerin, cetylpyridinium chloride, flavor, cinnamal, sodium saccharin, phosphoric acid, sodium benzoate, sucralose, poloxamer 407, benzoic acid, disodium phosphate, propylene glycol, red 33, green 3

Disclaimers

This rinse may cause temporary staining to the surface of teeth.

This is not harmful, and adequate brushing may prevent its occurrence.

*This product is not manufactured or distributed by Procter & Gamble, distributor of Crest® Pro-Health® Advanced Anticavity Fluoride Mouthwash Enamel Care Alcohol Free.

**This product is not intended to replace brushing or flossing.

Adverse reaction

"SATISFACTION GUARANTEED OR YOUR MONEY BACK."

Manufactured For Your Military Exchanges

By: Consumer Product Partners, LLC

St. Louis, MO 63114

principal display panel

ALCOHOL FREE

Compare To The Active Ingredients of Crest® Pro-Health® Advanced Anticavity Fluoride Mouthwash*

Exchange Select™

FLUORIDE MOUTHWASH

ANTICAVITY FLUORIDE RINSE

Violet Mint

- Kills bad breath germs
- Helps prevent cavities
- Helps strengthen enamel
- Cleans teeth**
- Freshens breath

IMPORANT: READ DIRECTIONS FOR PROPER USE

quality value

1 L (1.05 QT) 33.8 FL OZ